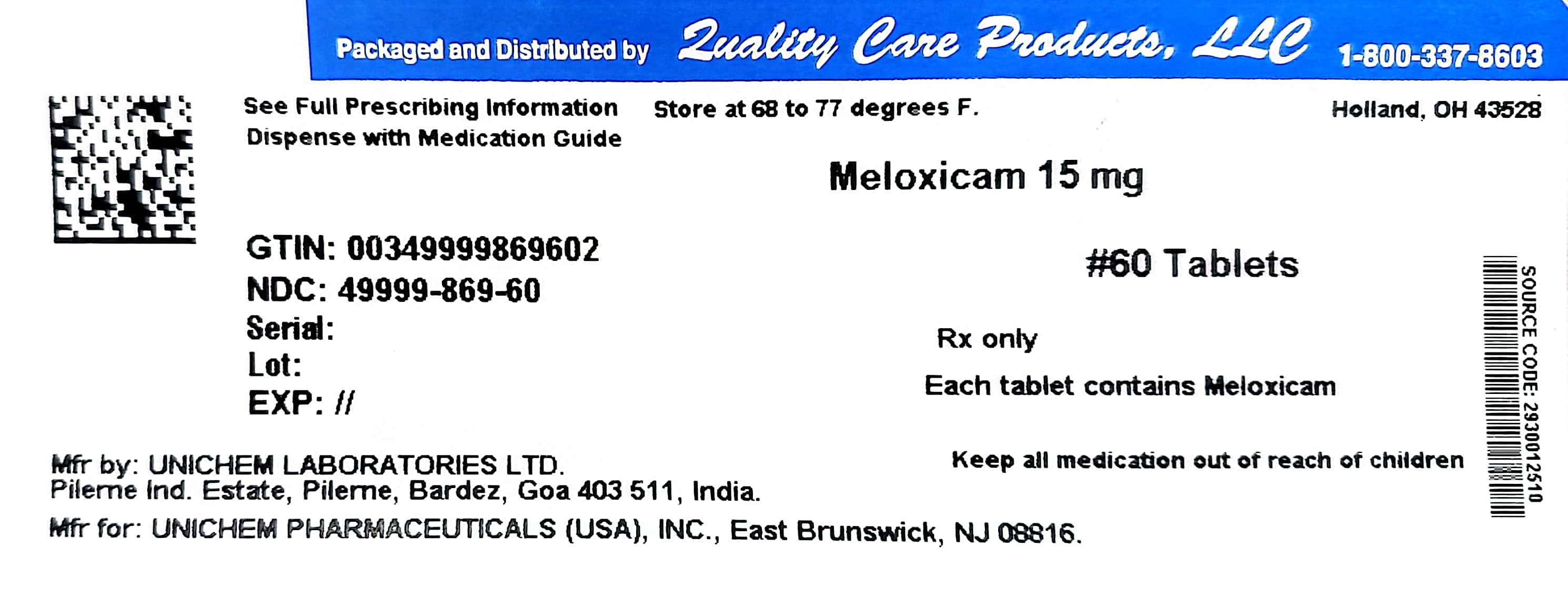 DRUG LABEL: Meloxicam
NDC: 49999-869 | Form: TABLET
Manufacturer: Quality Care Products LLC
Category: prescription | Type: HUMAN PRESCRIPTION DRUG LABEL
Date: 20241216

ACTIVE INGREDIENTS: MELOXICAM 15 mg/1 1
INACTIVE INGREDIENTS: SILICON DIOXIDE; CROSPOVIDONE; LACTOSE MONOHYDRATE; MAGNESIUM STEARATE; CELLULOSE, MICROCRYSTALLINE; POVIDONE

Meloxicam 15 mg

DESCRIPTION

Meloxicam, an oxicam derivative, is a member of the enolic acid group of nonsteroidal anti-inflammatory drugs (NSAIDs). Each pastel yellow Meloxicam tablet USP contains 7.5 mg or 15 mg meloxicam for oral administration. Meloxicam is chemically designated as 4-hydroxy-2-methyl-N-(5-methyl-2-thiazolyl)-2H-1,2-benzothiazine-3-carboxamide-1,1-dioxide. The molecular weight is 351.4. Its empirical formula is C14H13N3O4S2 and it has the following structural formula.
Meloxicam is a pastel yellow solid, practically insoluble in water, with higher solubility observed in strong acids and bases. It is very slightly soluble in methanol. Meloxicam has an apparent partition coefficient (log P)app = 0.1 in n-octanol/buffer pH 7.4. Meloxicam has pKa values of 1.1 and 4.2.

Meloxicam is available as a tablet for oral administration containing 7.5 mg or 15 mg meloxicam.

The inactive ingredients in Meloxicam tablets USP include colloidal silicon dioxide, crospovidone, lactose monohydrate, magnesium stearate, microcrystalline cellulose, povidone and sodium citrate dihydrate.

CLINICAL PHARMACOLOGY
Mechanism of Action

Meloxicam is a nonsteroidal anti-inflammatory drug (NSAID) that exhibits anti-inflammatory, analgesic, and antipyretic activities in animal models. The mechanism of action of meloxicam, like that of other NSAIDs, may be related to prostaglandin synthetase (cyclo-oxygenase) inhibition.

Pharmacokinetics

Absorption

The absolute bioavailability of meloxicam capsules was 89% following a single oral dose of 30 mg compared with 30 mg IV bolus injection. Following single intravenous doses, dose-proportional pharmacokinetics were shown in the range of 5 mg to 60 mg. After multiple oral doses the pharmacokinetics of meloxicam capsules were dose-proportional over the range of 7.5 mg to 15 mg. Mean Cmax was achieved within four to five hours after a 7.5 mg meloxicam tablet was taken under fasted conditions, indicating prolonged drug absorption. With multiple dosing, steady state concentrations were reached by Day 5. A second meloxicam concentration peak occurs around 12 to 14 hours post-dose suggesting biliary recycling.

INDICATIONS AND USAGE

Carefully consider the potential benefits and risks of meloxicam and other treatment options before deciding to use meloxicam. Use the lowest effective dose for the shortest duration consistent with individual patient treatment goals (see WARNINGS).

Meloxicam is indicated for relief of the signs and symptoms of osteoarthritis and rheumatoid arthritis.

CONTRAINDICATIONS

Meloxicam is contraindicated in patients with known hypersensitivity to meloxicam.

Meloxicam should not be given to patients who have experienced asthma, urticaria, or allergic-type reactions after taking aspirin or other NSAIDs. Severe, rarely fatal, anaphylactic-like reactions to NSAIDs have been reported in such patients (see WARNINGS, Anaphylactoid Reactions, and PRECAUTIONS, Pre-existing Asthma).

Meloxicam is contraindicated for the treatment of peri-operative pain in the setting of coronary artery bypass graft (CABG) surgery (see WARNINGS).

WARNINGS
Cardiovascular EffectsCardiovascular Thrombotic Events

Clinical trials of several COX-2 selective and nonselective NSAIDs of up to three years duration have shown an increased risk of serious cardiovascular (CV) thrombotic events, myocardial infarction, and stroke, which can be fatal. All NSAIDs, both COX-2 selective and nonselective, may have a similar risk. Patients with known CV disease or risk factors for CV disease may be at greater risk. To minimize the potential risk for an adverse CV event in patients treated with an NSAID, the lowest effective dose should be used for the shortest duration possible. Physicians and patients should remain alert for the development of such events, even in the absence of previous CV symptoms. Patients should be informed about the signs and/or symptoms of serious CV events and the steps to take if they occur.

There is no consistent evidence that concurrent use of aspirin mitigates the increased risk of serious CV thrombotic events associated with NSAID use. The concurrent use of aspirin and an NSAID does increase the risk of serious GI events (see WARNINGS, Gastrointestinal (GI) Effects - Risk of GI Ulceration, Bleeding, and Perforation).

Two large, controlled, clinical trials of a COX-2 selective NSAID for the treatment of pain in the first 10-14 days following CABG surgery found an increased incidence of myocardial infarction and stroke (see CONTRAINDICATIONS).

Hypertension

NSAIDs, including meloxicam can lead to onset of new hypertension or worsening of pre-existing hypertension, either of which may contribute to the increased incidence of CV events. Patients taking thiazides or loop diuretics may have impaired response to these therapies when taking NSAIDs. NSAIDs, including meloxicam should be used with caution in patients with hypertension. Blood pressure (BP) should be monitored closely during the initiation of NSAID treatment and throughout the course of therapy.

Congestive Heart Failure and Edema

Fluid retention and edema have been observed in some patients taking NSAIDs. Meloxicam should be used with caution in patients with fluid retention, hypertension, or heart failure.

Gastrointestinal (GI) Effects - Risk of GI Ulceration, Bleeding, and Perforation

NSAIDs, including meloxicam can cause serious gastrointestinal (GI) adverse events including inflammation, bleeding, ulceration, and perforation of the stomach, small intestine, or large intestine, which can be fatal. These serious adverse events can occur at any time, with or without warning symptoms, in patients treated with NSAIDs. Only one in five patients, who develop a serious upper GI adverse event on NSAID therapy, is symptomatic. Upper GI ulcers, gross bleeding, or perforation caused by NSAIDs, occur in approximately 1% of patients treated for 3-6 months, and in about 2-4% of patients treated for one year. These trends continue with longer duration of use, increasing the likelihood of developing a serious GI event at some time during the course of therapy. However, even short-term therapy is not without risk.

NSAIDs should be prescribed with extreme caution in those with a prior history of ulcer disease or gastrointestinal bleeding. Patients with a prior history of peptic ulcer disease and/or gastrointestinal bleeding who use NSAIDs have a greater than 10-fold increased risk for developing a GI bleed compared to patients with neither of these risk factors. Other factors that increase the risk for GI bleeding in patients treated with NSAIDs include concomitant use of oral corticosteroids or anticoagulants, longer duration of NSAID therapy, smoking, use of alcohol, older age, and poor general health status. Most spontaneous reports of fatal GI events are in elderly or debilitated patients and therefore, special care should be taken in treating this population.

To minimize the potential risk for an adverse GI event in patients treated with an NSAID, the lowest effective dose should be used for the shortest possible duration. Patients and physicians should remain alert for signs and symptoms of GI ulceration and bleeding during NSAID therapy and promptly initiate additional evaluation and treatment if a serious GI adverse event is suspected. This should include discontinuation of the NSAID until a serious GI adverse event is ruled out. For high-risk patients, alternate therapies that do not involve NSAIDs should be considered.

Renal Effects

Long-term administration of NSAIDs including meloxicam can result in renal papillary necrosis, renal insufficiency, acute renal failure, and other renal injury. Renal toxicity has also been seen in patients in whom renal prostaglandins have a compensatory role in the maintenance of renal perfusion. In these patients, administration of a nonsteroidal anti-inflammatory drug may cause a dose-dependent reduction in prostaglandin formation and, secondarily, in renal blood flow, which may precipitate overt renal decompensation. Patients at greatest risk of this reaction are those with impaired renal function, heart failure, liver dysfunction, those taking diuretics and ACE inhibitors, angiotensin II receptor antagonists, and the elderly. Discontinuation of NSAID therapy is usually followed by recovery to the pretreatment state.

Advanced Renal Disease

No information is available from controlled clinical studies regarding the use of meloxicam in patients with advanced renal disease. Therefore, treatment with meloxicam is not recommended in these patients with advanced renal disease. If meloxicam therapy must be initiated, close monitoring of the patient's renal function is advisable.

Anaphylactoid Reactions

As with other NSAIDS, anaphylactoid reactions have occurred in patients without known prior exposure to meloxicam. Meloxicam should not be given to patients with the aspirin triad. This symptom complex typically occurs in asthmatic patients who experience rhinitis with or without nasal polyps, or who exhibit severe, potentially fatal bronchospasm after taking aspirin or other NSAIDs (see CONTRAINDICATIONS and PRECAUTIONS, Pre-existing Asthma). Emergency help should be sought in cases where an anaphylactoid reaction occurs.

Skin Reactions

NSAIDs, including meloxicam can cause serious skin adverse events such as exfoliative dermatitis, Stevens - Johnson syndrome (SJS), and toxic epidermal necrolysis (TEN), which can be fatal. These serious events may occur without warning. Patients should be informed about the signs and symptoms of serious skin manifestations and use of the drug should be discontinued at the first appearance of skin rash or any other sign of hypersensitivity.

Pregnancy

In late pregnancy, as with other NSAIDs, meloxicam should be avoided because it may cause premature closure of the ductus arteriosus.

PRECAUTIONS
General

Meloxicam cannot be expected to substitute for corticosteroids or to treat corticosteroid insufficiency. Abrupt discontinuation of corticosteroids may lead to disease exacerbation. Patients on prolonged corticosteroid therapy should have their therapy tapered slowly if a decision is made to discontinue corticosteroids.

The pharmacological activity of meloxicam in reducing fever and inflammation may diminish the utility of these diagnostic signs in detecting complications of presumed noninfectious, painful conditions.

Hepatic Effects

Borderline elevations of one or more liver tests may occur in up to 15% of patients taking NSAIDs including meloxicam. These laboratory abnormalities may progress, may remain unchanged, or may be transient with continuing therapy. Notable elevations of ALT or AST (approximately three or more times the upper limit of normal) have been reported in approximately 1% of patients in clinical trials with NSAIDs. In addition, rare cases of severe hepatic reactions, including jaundice and fatal fulminant hepatitis, liver necrosis and hepatic failure, some of them with fatal outcomes have been reported.

A patient with symptoms and/or signs suggesting liver dysfunction, or in whom an abnormal liver test has occurred, should be evaluated for evidence of the development of a more severe hepatic reaction while on therapy with meloxicam. If clinical signs and symptoms consistent with liver disease develop, or if systemic manifestations occur (e.g., eosinophilia, rash, etc.), meloxicam should be discontinued.

Renal Effects

Caution should be used when initiating treatment with meloxicam in patients with considerable dehydration. It is advisable to rehydrate patients first and then start therapy with meloxicam. Caution is also recommended in patients with pre-existing kidney disease (see WARNINGS, Renal Effects and Advanced Renal Disease).

The extent to which metabolites may accumulate in patients with renal failure has not been studied with meloxicam. Because some meloxicam metabolites are excreted by the kidney, patients with significantly impaired renal function should be more closely monitored.

Hematological Effects

Anemia is sometimes seen in patients receiving NSAIDs, including meloxicam. This may be due to fluid retention, occult or gross GI blood loss, or an incompletely described effect upon erythropoiesis. Patients on long-term treatment with NSAIDs, including meloxicam, should have their hemoglobin or hematocrit checked if they exhibit any signs or symptoms of anemia.

Drugs which inhibit the biosynthesis of prostaglandins may interfere to some extent with platelet function and vascular responses to bleeding.

NSAIDs inhibit platelet aggregation and have been shown to prolong bleeding time in some patients. Unlike aspirin their effect on platelet function is quantitatively less, of shorter duration, and reversible. Patients receiving meloxicam who may be adversely affected by alterations in platelet function, such as those with coagulation disorders or patients receiving anticoagulants should be carefully monitored.

Pre-existing Asthma

Patients with asthma may have aspirin-sensitive asthma. The use of aspirin in patients with aspirin-sensitive asthma has been associated with severe bronchospasm which can be fatal. Since cross reactivity, including bronchospasm, between aspirin and other NSAIDs has been reported in such aspirin-sensitive patients, meloxicam should not be administered to patients with this form of aspirin sensitivity and should be used with caution in patients with pre-existing asthma.

ADVERSE REACTIONS

Enter section text here

OVERDOSAGE

There is limited experience with meloxicam overdose. Four cases have taken 6 to 11 times the highest recommended dose; all recovered. Cholestyramine is known to accelerate the clearance of meloxicam.

Symptoms following acute NSAID overdose are usually limited to lethargy, drowsiness, nausea, vomiting, and epigastric pain, which are generally reversible with supportive care. Gastrointestinal bleeding can occur. Severe poisoning may result in hypertension, acute renal failure, hepatic dysfunction, respiratory depression, coma, convulsions, cardiovascular collapse, and cardiac arrest. Anaphylactoid reactions have been reported with therapeutic ingestion of NSAIDs, and may occur following an overdose.

Patients should be managed with symptomatic and supportive care following an NSAID overdose. In cases of acute overdose, gastric lavage followed by activated charcoal is recommended. Gastric lavage performed more than one hour after overdose has little benefit in the treatment of overdose. Administration of activated charcoal is recommended for patients who present 1-2 hours after overdose. For substantial overdose or severely symptomatic patients, activated charcoal may be administered repeatedly. Accelerated removal of meloxicam by 4 gm oral doses of cholestyramine given three times a day was demonstrated in a clinical trial. Administration of cholestyramine may be useful following an overdose. Forced diuresis, alkalinization of urine, hemodialysis, or hemoperfusion may not be useful due to high protein binding.

DOSAGE AND ADMINISTRATIONOsteoarthritis and Rheumatoid Arthritis

Carefully consider the potential benefits and risks of meloxicam and other treatment options before deciding to use meloxicam. Use the lowest effective dose for the shortest duration consistent with individual patient treatment goals (see WARNINGS).

After observing the response to initial therapy with meloxicam, the dose should be adjusted to suit an individual patient's needs.

For the relief of the signs and symptoms of osteoarthritis the recommended starting and maintenance oral dose of meloxicam is 7.5 mg once daily. Some patients may receive additional benefit by increasing the dose to 15 mg once daily. For the relief of the signs and symptoms of rheumatoid arthritis, the recommended starting and maintenance oral dose of meloxicam is 7.5 mg once daily. Some patients may receive additional benefit by increasing the dose to 15 mg once daily.

The maximum recommended daily oral dose of meloxicam is 15 mg.

Meloxicam may be taken without regard to timing of meals.

HOW SUPPLIED

Meloxicam Tablets USP are available as light yellow, round, flat, uncoated tablets containing meloxicam 7.5 mg or as light yellow, oblong, biconvex, uncoated tablets containing meloxicam 15 mg. The 7.5 mg tablet is impressed with letter U and L on one side and tablet code 7.5 on the other side. The 15 mg tablet is impressed with letter U and L on one side and tablet code 15 on the other side.

Meloxicam Tablets USP 7.5 mg are available as follows:

Meloxicam Tablets USP 15 mg are available as follows:

49999-869-15

49999-869-30

49999-869-60

49999-869-90

Information for Patients

Patients should be informed of the following information before initiating therapy with an NSAID and periodically during the course of ongoing therapy. Patients should also be encouraged to read the NSAID Medication Guide that accompanies each prescription dispensed.

1. Meloxicam, like other NSAIDs, may cause serious CV side effects, such as MI or stroke, which may result in hospitalization and even death. Although serious CV events can occur without warning symptoms, patients should be alert for the signs and symptoms of chest pain, shortness of breath, weakness, slurring of speech, and should ask for medical advice when observing any indicative sign or symptoms. Patients should be apprised of the importance of this follow-up (see WARNINGS, Cardiovascular Effects).
2. Meloxicam, like other NSAIDs, can cause GI discomfort and, rarely, serious GI side effects, such as ulcers and bleeding, which may result in hospitalization and even death. Although serious GI tract ulcerations and bleeding can occur without warning symptoms, patients should be alert for the signs and symptoms of ulcerations and bleeding, and should ask for medical advice when observing any indicative sign or symptoms including epigastric pain, dyspepsia, melena, and hematemesis. Patients should be apprised of the importance of this follow-up (see WARNINGS, Gastrointestinal (GI) Effects - Risk of GI Ulceration, Bleeding, and Perforation).
3. Meloxicam, like other NSAIDs, can cause serious skin side effects such as exfoliative dermatitis, SJS, and TEN, which may result in hospitalizations and even death. Although serious skin reactions may occur without warning, patients should be alert for the signs and symptoms of skin rash and blisters, fever, or other signs of hypersensitivity such as itching, and should ask for medical advice when observing any indicative signs or symptoms. Patients should be advised to stop the drug immediately if they develop any type of rash and contact their physicians as soon as possible.
4. Patients should promptly report signs or symptoms of unexplained weight gain or edema to their physicians.
5. Patients should be informed of the warning signs and symptoms of hepatotoxicity (e.g., nausea, fatigue, lethargy, pruritus, jaundice, right upper quadrant tenderness, and "flu-like" symptoms). If these occur, patients should be instructed to stop therapy and seek immediate medical therapy.
6. Patients should be informed of the signs of an anaphylactoid reaction (e.g., difficulty breathing, swelling of the face or throat). If these occur, patients should be instructed to seek immediate emergency help (see WARNINGS).
7. In late pregnancy, as with other NSAIDs, meloxicam should be avoided because it will cause premature closure of the ductus arteriosus.

Laboratory Tests

Because serious GI tract ulcerations and bleeding can occur without warning symptoms, physicians should monitor for signs or symptoms of GI bleeding. Patients on long-term treatment with NSAIDs should have their CBC and a chemistry profile checked periodically. If clinical signs and symptoms consistent with liver or renal disease develop, systemic manifestations occur (e.g., eosinophilia, rash, etc.) or if abnormal liver tests persist or worsen, meloxicam should be discontinued.

Drug InteractionsACE-inhibitors

Reports suggest that NSAIDs may diminish the antihypertensive effect of ACE-inhibitors. This interaction should be given consideration in patients taking NSAIDs concomitantly with ACE inhibitors.

Aspirin

When meloxicam is administered with aspirin (1000 g TID) to healthy volunteers, it tended to increase the AUC (10%) and Cmax (24%) of meloxicam. The clinical significance of this interaction is not known; however, as with other NSAIDs concomitant administration of meloxicam and aspirin is not generally recommended because of the potential for increased adverse effects.

Concomitant administration of low-dose aspirin with meloxicam may result in an increased rate of GI ulceration or other complications, compared to use of meloxicam alone. Meloxicam is not a substitute for aspirin for cardiovascular prophylaxis.

Cholestyramine

Pretreatment for four days with cholestyramine significantly increased the clearance of meloxicam by 50%. This resulted in a decrease in t1/2, from 19.2 hours to 12.5 hours, and a 35% reduction in AUC. This suggests the existence of a recirculation pathway for meloxicam in the gastrointestinal tract. The clinical relevance of this interaction has not been established.

Cimetidine

Concomitant administration of 200 mg cimetidine QID did not alter the single-dose pharmacokinetics of 30 mg meloxicam.

Digoxin

Meloxicam 15 mg once daily for 7 days did not alter the plasma concentration profile of digoxin after β-acetyldigoxin administration for 7 days at clinical doses. In vitro testing found no protein binding drug interaction between digoxin and meloxicam.

Furosemide

Clinical studies, as well as post-marketing observations, have shown that NSAIDs can reduce the natriuretic effect of furosemide and thiazides in some patients. This response has been attributed to inhibition of renal prostaglandin synthesis. Studies with furosemide agents and meloxicam have not demonstrated a reduction in natriuretic effect. Furosemide single and multiple dose pharmacodynamics and pharmacokinetics are not affected by multiple doses of meloxicam. Nevertheless, during concomitant therapy with meloxicam, patients should be observed closely for signs of renal failure (see WARNINGS, Renal Effects), as well as to assure diuretic efficacy.

Lithium

In a study conducted in healthy subjects, mean pre-dose lithium concentration and AUC were increased by 21% in subjects receiving lithium doses ranging from 804 to 1072 mg BID with meloxicam 15 mg QD as compared to subjects receiving lithium alone. These effects have been attributed to inhibition of renal prostaglandin synthesis by meloxicam. Patients on lithium treatment should be closely monitored for signs of lithium toxicity when meloxicam is introduced, adjusted, or withdrawn.

Methotrexate

NSAIDs have been reported to competitively inhibit methotrexate accumulation in rabbit kidney slices. This may indicate that they could enhance the toxicity of methotrexate. Caution should be used when NSAIDs are administered concomitantly with methotrexate.

A study in 13 rheumatoid arthritis (RA) patients evaluated the effects of multiple doses of meloxicam on the pharmacokinetics of methotrexate taken once weekly. Meloxicam did not have a significant effect on the pharmacokinetics of single doses of methotrexate.In vitro, methotrexate did not displace meloxicam from its human serum binding sites.

Warfarin

The effects of warfarin and NSAIDs on GI bleeding are synergistic, such that users of both drugs together have a risk of serious GI bleeding higher than users of either drug alone.

Anticoagulant activity should be monitored, particularly in the first few days after initiating or cha nging meloxicam therapy in patients receiving warfarin or similar agents, since these patients are at an increased risk of bleeding. The effect of meloxicam on the anticoagulant effect of warfarin was studied in a group of healthy subjects receiving daily doses of warfarin that produced an INR (International Normalized Ratio) between 1.2 and 1.8. In these subjects, meloxicam did not alter warfarin pharmacokinetics and the average anticoagulant effect of warfarin as determined by prothrombin time. However, one subject showed an increase in INR from 1.5 to 2.1. Caution should be used when administering meloxicam with warfarin since patients on warfarin may experience changes in INR and an increased risk of bleeding complications when a new medication is introduced.

Carcinogenesis, Mutagenesis, Impairment of Fertility

No carcinogenic effect of meloxicam was observed in rats given oral doses up to 0.8 mg/kg/day (approximately 0.4-fold the human dose at 15 mg/day for a 50 kg adult based on body surface area conversion) for 104 weeks or in mice given oral doses up to 8.0 mg/kg/day (approximately 2.2-fold the human dose, as noted above) for 99 weeks.

Meloxicam was not mutagenic in an Ames assay, or clastogenic in a chromosome aberration assay with human lymphocytes and an in vivo micronucleus test in mouse bone marrow.

Meloxicam did not impair male and female fertility in rats at oral doses up to 9 and 5 mg/kg/day, respectively (4.9-fold and 2.5-fold the human dose, as noted above). However, an increased incidence of embryolethality at oral doses ≥1 mg/kg/day (0.5-fold the human dose, as noted above) was observed in rats when dams were given meloxicam 2 weeks prior to mating and during early embryonic development.

Pregnancy

Teratogenic Effects: Pregnancy Category C.

Meloxicam caused an increased incidence of septal defect of the heart, a rare event, at an oral dose of 60 mg/kg/day (64.5-fold the human dose at 15 mg/day for a 50 kg adult based on body surface area conversion) and embryolethality at oral doses ≥5 mg/kg/day (5.4-fold the human dose, as noted above) when rabbits were treated throughout organogenesis. Meloxicam was not teratogenic in rats up to an oral dose of 4 mg/kg/day (approximately 2.2-fold the human dose, as noted above) throughout organogenesis. An increased incidence of stillbirths was observed when rats were given oral doses ≥1 mg/kg/day throughout organogenesis. Meloxicam crosses the placental barrier. There are no adequate and well-controlled studies in pregnant women. Meloxicam should be used during pregnancy only if the potential benefit justifies the potential risk to the fetus.

Nonteratogenic Effects

Because of the known effects of nonsteroidal antiinflammatory drugs on the fetal cardiovascular system (closure of ductus arteriosus), use during pregnancy (particularly late pregnancy) should be avoided.

Meloxicam caused a reduction in birth index, live births, and neonatal survival at oral doses ≥0.125 mg/kg/day (approximately 0.07-fold the human dose at 15 mg/day for a 50 kg adult based on body surface area conversion) when rats were treated during the late gestation and lactation period. No studies have been conducted to evaluate the effect of meloxicam on the closure of the ductus arteriosus in humans; use of meloxicam during the third trimester of pregnancy should be avoided.

Labor and Delivery

Studies in rats with meloxicam, as with other drugs known to inhibit prostaglandin synthesis, showed an increased incidence of stillbirths, prolonged delivery, and delayed parturition at oral dosages ≥1 mg/kg/day (approximately 0.5-fold the human dose at 15 mg/day for a 50 kg adult based on body surface area conversion), and decreased pup survival at an oral dose of 4 mg/kg/day (approximately 2.1-fold the human dose, as noted above) throughout organogenesis. Similar findings were observed in rats receiving oral dosages ≥0.125 mg/kg/day (approximately 0.07-fold the human dose, as noted above) during late gestation and the lactation period.

The effects of meloxicam on labor and delivery in pregnant women are unknown.

Nursing Mothers

It is not known whether this drug is excreted in human milk however, meloxicam was excreted in the milk of lactating rats at concentrations higher than those in plasma. Because many drugs are excreted in human milk and because of the potential for serious adverse reactions in nursing infants from meloxicam, a decision should be made whether to discontinue nursing or to discontinue the drug, taking into account the importance of the drug to the mother.

Pediatric Use

Use of this drug for a pediatric indication is protected by marketing exclusivity.

Geriatric Use

As with any NSAID, caution should be exercised in treating the elderly (65 years and older).

BOXED WARNING

Cardiovascular Risk

- NSAIDs may cause an increased risk of serious cardiovascular thrombotic events, myocardial infarction, and stroke, which can be fatal. This risk may increase with duration of use. Patients with cardiovascular disease or risk factors for cardiovascular disease may be at greater risk (see WARNINGS and CLINICAL TRIALS).
- Meloxicam is contraindicated for the treatment of peri-operative pain in the setting of coronary artery bypass graft (CABG) surgery (see WARNINGS).

Gastrointestinal Risk

- NSAIDs cause an increased risk of serious gastrointestinal adverse events including bleeding, ulceration, and perforation of the stomach or intestines, which can be fatal. These events can occur at any time during use and without warning symptoms. Elderly patients are at greater risk for serious gastrointestinal events (see WARNINGS).

MEDICATION GUIDE

MELOXICAM - meloxicam tablet
Unichem Pharmaceuticals (USA), Inc.

----------

Meloxicam Tablets USP 7.5 mg and 15 mg

Meloxicam Tablets USP 7.5 mg and 15 mg

Medication Guide for Non-Steroidal Anti-Inflammatory Drugs (NSAIDs)

(See the end of this Medication Guide for a list of prescription NSAID medicines).

What is the most important information I should know about medicines called Non-Steroidal Anti-Inflammatory Drugs (NSAIDs)?

NSAID medicines may increase the chance of a heart attack or stroke that can lead to death. This chance increases:

- with longer use of NSAID medicines
- in people who have heart disease

NSAID medicines should never be used right before or after a heart surgery called a "coronary artery bypass graft (CABG)."

NSAID medicines can cause ulcers and bleeding in the stomach and intestines at any time during treatment. Ulcers and bleeding:

- can happen without warning symptoms
- may cause death

The chance of a person getting an ulcer or bleeding increases with:

- taking medicines called "corticosteroids" and "anticoagulants"
- longer use
- smoking
- drinking alcohol
- older age
- having poor health

NSAID medicines should only be used:

- exactly as prescribed
- at the lowest dose possible for your treatment
- for the shortest time needed

What are Non-Steroidal Anti-Inflammatory Drugs (NSAIDs)?

NSAID medicines are used to treat pain and redness, swelling, and heat (inflammation) from medical conditions such as:

- different types of arthritis
- menstrual cramps and other types of short-term pain

Who should not take a Non-Steroidal Anti-Inflammatory Drug (NSAID)?

Do not take an NSAID medicine:

- if you had an asthma attack, hives, or other allergic reaction with aspirin or any other NSAID medicine
- for pain right before or after heart bypass surgery

Tell your healthcare provider:

- about all of your medical conditions
- about all of the medicines you take. NSAIDs and some other medicines can interact with each other and cause serious side effects. Keep a list of your medicines to show to your healthcare provider and pharmacist
- if you are pregnant. NSAID medicines should not be used by pregnant women late in their pregnancy
- if you are breastfeeding. Talk to your doctor

Get emergency help right away if you have any of the following symptoms:

- shortness of breath or trouble breathing
- chest pain
- weakness in one part or side of your body
- slurred speech
- Swelling of the face or throat

Stop your NSAID medicine and call your healthcare provider right away if you have any of the following symptoms:

- nausea
- more tired or weaker than usual
- itching
- your skin or eyes look yellow
- stomach pain
- flu-like symptoms
- vomit blood
- there is blood in your bowel movement or it is black and sticky like tar
- skin rash or blisters with fever
- unusual weight gain
- swelling of the arms and legs, hands and feet

These are not all the side effects with NSAID medicines. Talk to your healthcare provider or pharmacist for more information about NSAID medicines.

Call your doctor for medical advice about side effects. You may report side effects to FDA at 1-800-FDA-1088.

Other information about Non-Steroidal Anti-Inflammatory Drugs (NSAIDs)

Aspirin is an NSAID medicine but it does not increase the chance of a heart attack. Aspirin can cause bleeding in the brain, stomach, and intestines. Aspirin can also cause ulcers in the stomach and intestines. Some of these NSAID medicines are sold in lower doses without a prescription (over-the-counter). Talk to your healthcare provider before using over-the-counter NSAIDs for more than 10 days.

NSAID medicines that need a prescription

Revised: 02/2009Unichem Pharmaceuticals (USA), Inc.